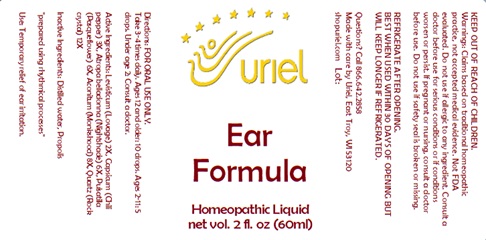 DRUG LABEL: Ear Formula
NDC: 48951-4011 | Form: LIQUID
Manufacturer: Uriel Pharmacy Inc.
Category: homeopathic | Type: HUMAN OTC DRUG LABEL
Date: 20240426

ACTIVE INGREDIENTS: LEVISTICUM OFFICINALE ROOT 2 [hp_X]/1 mL; PAPRIKA 3 [hp_X]/1 mL; ATROPA BELLADONNA 6 [hp_X]/1 mL; PULSATILLA VULGARIS 6 [hp_X]/1 mL; ACONITUM NAPELLUS 8 [hp_X]/1 mL; SILICON DIOXIDE 12 [hp_X]/1 mL
INACTIVE INGREDIENTS: PROPOLIS WAX; WATER

Ear Formula

INDICATIONS AND USAGE

Directions: FOR ORAL USE ONLY.

DOSAGE AND ADMINISTRATION

Take 3-4 times daily. Ages 12 and older: 10 drops. Ages 2-11: 5 drops. Under age 2: Consult a doctor.

ACTIVE INGREDIENT

Active Ingredients: Levisticum (Lovage) 2X, Capsicum (Chili pepper) 3X, Atropa belladonna (Nightshade) 6X, Pulsatilla (Pasqueflower) 6X, Aconitum (Monkshood) 8X, Quartz (Rock crystal) 12X

Inactive Ingredients: Distilled water, Propolis

"prepared using rhythmical processes"

PURPOSE

Use: Temporary relief of ear irritation.

KEEP OUT OF REACH OF CHILDREN.

WARNINGS

Warnings: Claims based on traditional homeopathic practice, not accepted medical evidence. Not FDA evaluated. Do not use if allergic to any ingredient. Consult a doctor before use for serious conditions or if conditions worsen or persist. If pregnant or nursing, consult a doctor before use. Do not use if safety seal is broken or missing.

REFRIGERATE AFTER OPENING.
BEST WHEN USED WITHIN 30 DAYS OF OPENING BUT WILL KEEP LONGER IF REFRIGERATED.

QUESTIONS

Questions? Call 866.642.2858 Made with care by Uriel, East Troy, WI 53120 shopuriel.com Lot: